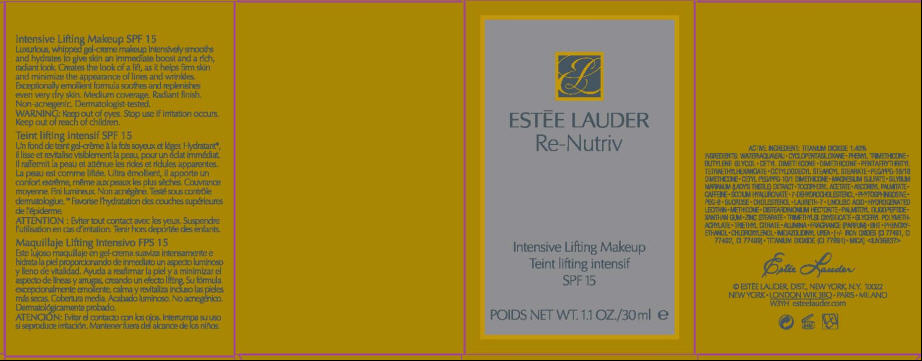 DRUG LABEL: RE-NUTRIV 
NDC: 11559-769 | Form: CREAM
Manufacturer: ESTEE LAUDER INC
Category: otc | Type: HUMAN OTC DRUG LABEL
Date: 20110919

ACTIVE INGREDIENTS: TITANIUM DIOXIDE 1.4 mL/100 mL
INACTIVE INGREDIENTS: WATER; CYCLOMETHICONE 5; PHENYL TRIMETHICONE; BUTYLENE GLYCOL; DIMETHICONE; PENTAERYTHRITYL TETRAETHYLHEXANOATE; OCTYLDODECYL STEAROYL STEARATE; MAGNESIUM SULFATE, UNSPECIFIED; MILK THISTLE; ALPHA-TOCOPHEROL ACETATE; ASCORBYL PALMITATE; CAFFEINE; HYALURONATE SODIUM; 7-DEHYDROCHOLESTEROL; POLYETHYLENE GLYCOL 400; SUCROSE; CHOLESTEROL; LAURETH-7; LINOLEIC ACID; HYDROGENATED SOYBEAN LECITHIN; PALMITOYL OLIGOPEPTIDE; XANTHAN GUM; ZINC STEARATE; TRIETHYL CITRATE; ALUMINUM OXIDE; BUTYLATED HYDROXYTOLUENE; PHENOXYETHANOL; CHLOROXYLENOL; IMIDUREA; FERRIC OXIDE RED; FERRIC OXIDE YELLOW; FERROSOFERRIC OXIDE; MICA

ESTĒE LAUDER
Re-Nutriv

WARNING

WHEN USING

Keep out of eyes.

Stop use if irritation occurs.

Keep out of reach of children.

ACTIVE INGREDIENT

TITANIUM DIOXIDE 1.40%

INGREDIENTS

WATER\AQUA\EAU • CYCLOPENTASILOXANE • PHENYL TRIMETHICONE • BUTYLENE GLYCOL • CETYL DIMETHICONE • DIMETHICONE • PENTAERYTHRITYL TETRAETHYLHEXANOATE • OCTYLDODECYL STEAROYL STEARATE • PEG/PPG-18/18 DIMETHICONE • CETYL PEG/PPG-10/1 DIMETHICONE • MAGNESIUM SULFATE • SILYBUM MARIANUM (LADY'S THISTLE) EXTRACT • TOCOPHERYL ACETATE • ASCORBYL PALMITATE • CAFFEINE • SODIUM HYALURONATE • 7-DEHYDROCHOLESTEROL • PHYTOSPHINGOSINE • PEG-8 • SUCROSE • CHOLESTEROL • LAURETH-7 • LINOLEIC ACID • HYDROGENATED LECITHIN • METHICONE • DISTEARDIMONIUM HECTORITE • PALMITOYL OLIGOPEPTIDE • XANTHAN GUM • ZINC STEARATE • TRIMETHYLSILOXYSILICATE • GLYCERYL POLYMETHACRYLATE • TRIETHYL CITRATE • ALUMINA • FRAGRANCE (PARFUM) • BHT • PHENOXYETHANOL • CHLOROXYLENOL • IMIDAZOLIDINYL UREA • [+/- IRON OXIDES (CI 77491, CI 77492, CI 77499) • TITANIUM DIOXIDE (CI 77891) • MICA] <ILN36837>

PRINCIPAL DISPLAY PANEL - 30 ml CARTON

ESTĒE LAUDER
Re-Nutriv

Intensive Lifting Makeup
SPF 15

POIDS NET WT. 1.1 OZ./30 ml e